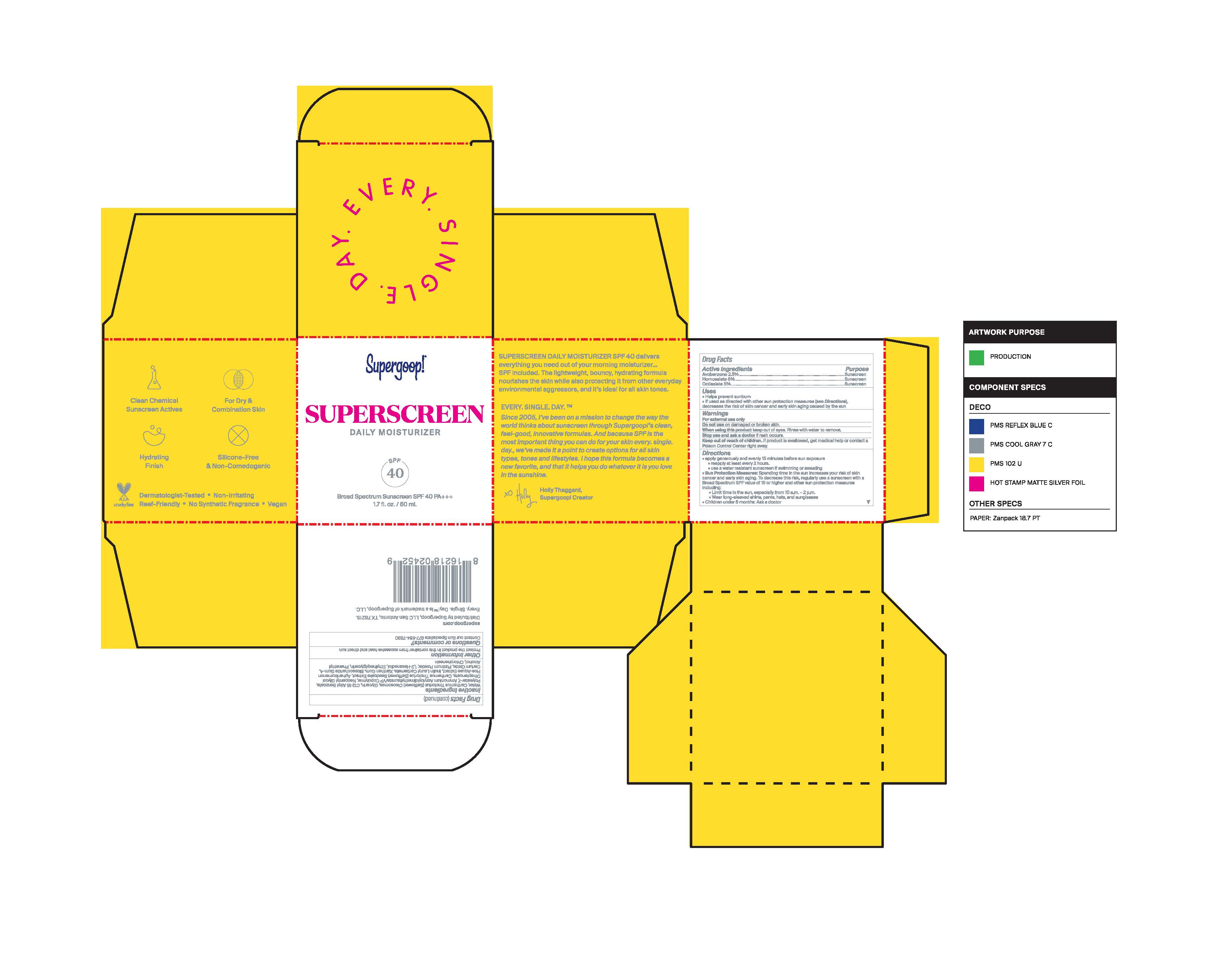 DRUG LABEL: SuperScreen Daily Moisturizer Broad Spectrum SPF 40
NDC: 75936-506 | Form: LOTION
Manufacturer: Supergoop, LLC
Category: otc | Type: HUMAN OTC DRUG LABEL
Date: 20241204

ACTIVE INGREDIENTS: AVOBENZONE 8 g/100 mL; OCTISALATE 5 g/100 mL; HOMOSALATE 8 g/100 mL
INACTIVE INGREDIENTS: POLYESTER-7; AMMONIUM ACRYLOYLDIMETHYLTAURATE/VP COPOLYMER; NEOPENTYL GLYCOL DIHEPTANOATE; CARTHAMUS TINCTORIUS SEEDCAKE; CERIC OXIDE; WATER; XANTHAN GUM; PLATINUM; 1,2-HEXANEDIOL; ETHYLHEXYLGLYCERIN; CHLORPHENESIN; APHANIZOMENON FLOSAQUAE; BIOSACCHARIDE GUM-4; PHENYLETHYL ALCOHOL; CARTHAMUS TINCTORIUS SEED OLEOSOMES; GLYCERIN; ALKYL (C12-15) BENZOATE

Superscreen Daily Moisturizer Broad Spectrum SPF 40

Active Ingredients Purpose

Avobenzone 2.5% Sunscreen

Homosalate 8% Sunscreen

Octisalate 5% Sunscreen

Uses

- Helps prevent Sunburn
- If used as directed with other sun Protection measures (see Directions), decreases the risk of skin cancer and early skin aging caused bu the sun.

Keep out of reach of children. If product is swallowed, get medical help or contact a Poison Control Center right away.

Stop use and ask a doctor and ask a doctor if rash occurs.

Warnings

For external use only

Do not use on damaged or broken skin

When using this product keep out of eyes. Rinse with water to remove.

Directions

- apply generously and evenly 15 minutes before sun exposure
- reapply at least every 2 hours
- Use a water resistant sunscreen if swimming or sweating
- Sun Protection Measure Spending time in the sun increases your risk of skin cancer and early skin aging. To decrease this risk, regularly use a sunscreen with a Broad Spectrum value of 15 or higher and other sun protection measures including:
- Limit time in the sun, especially from 10 a.m. - 2p.m.
- Wear Long-sleeved shirts, pants hats and sunglasses
- Children under 6 months ask a doctor

INACTIVE INGREDIENT

Inactive ingredients Water, Cartamus Tinctorius (safflower) Olesomes, Glycerin, C12-15 Alkyl Benzoate, Polyester-7, Ammonium Acryloyldimethyldimethyltaurate/VP Copolymer, Neopentyl Glycol Diheptanoate, Carthamus Tinctorius (Safflower) Seedcake extract, Aphanizomenon Flos-Aquae Extract, Inulin Lauryl Carbamate, Xanthan Gum, Biosaccharide Gum-4, Cerium Oxide, Platinum Powder, 1,2-hexanediol, Ehtylhexylglycerin, Phenethyl Alcohol, Chlorphenesin

PACKAGE LABEL

Supergoop!

Sunscreen Daily Moisturizer SPF 40

Broad Spectrum Sunscreen

1.7 fl oz / 50ml